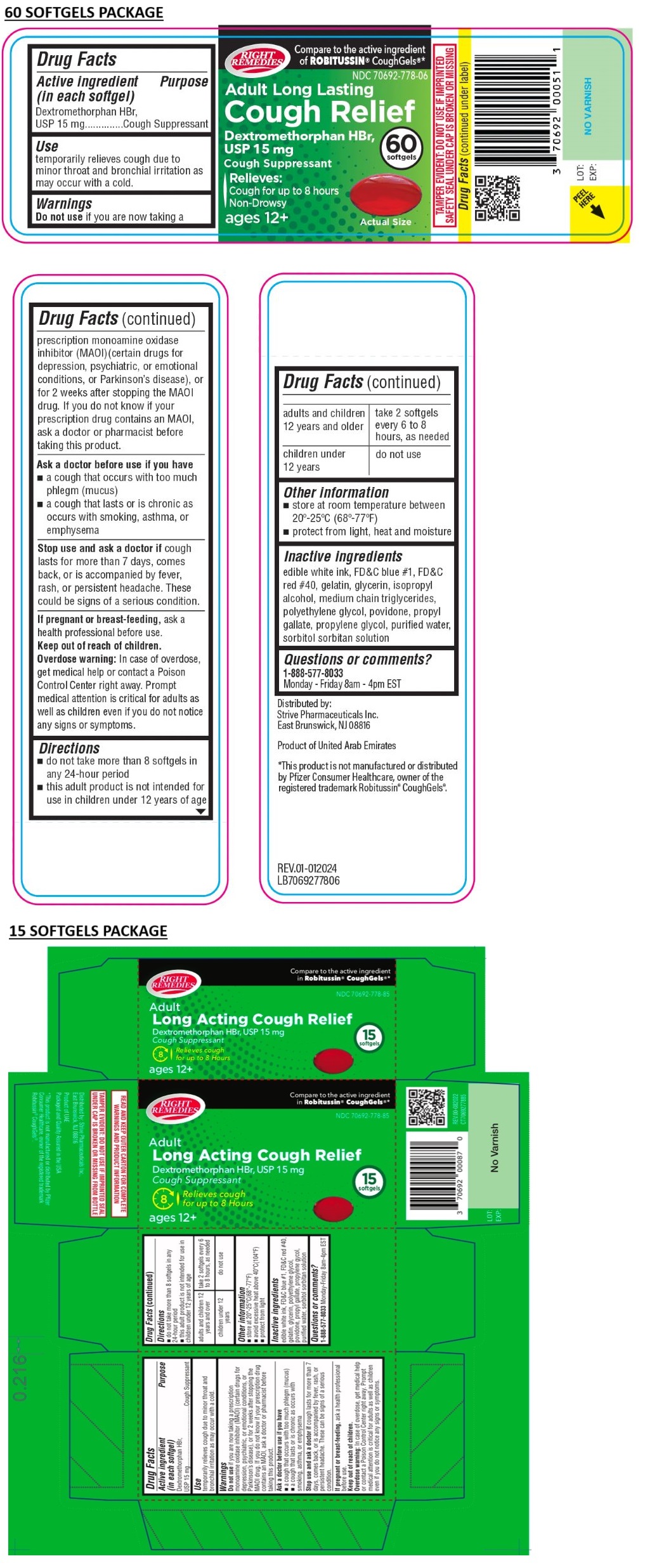 DRUG LABEL: Right Remedies Adult Long Lasting Cough Relief Softgel
NDC: 70692-778 | Form: CAPSULE
Manufacturer: Strive Pharmaceuticals Inc.
Category: otc | Type: HUMAN OTC DRUG LABEL
Date: 20250102

ACTIVE INGREDIENTS: DEXTROMETHORPHAN HYDROBROMIDE 15 mg/1 1
INACTIVE INGREDIENTS: FD&C BLUE NO. 1; FD&C RED NO. 40; GELATIN, UNSPECIFIED; GLYCERIN; ISOPROPYL ALCOHOL; MEDIUM-CHAIN TRIGLYCERIDES; POLYETHYLENE GLYCOL, UNSPECIFIED; POVIDONE, UNSPECIFIED; PROPYL GALLATE; PROPYLENE GLYCOL; WATER; SORBITOL; SORBITAN

RIGHT REMEDIES Adult Long Lasting Cough Relief Softgel

Active ingredient (in each softgel)

Dextromethorphan HBr, USP 15 mg

Purpose

Cough Suppressant

Use

temporarily relieves cough due to minor throat and bronchial irritation as may occur with a cold.

Warnings

Do not use if you are now taking a prescription monoamine oxidase inhibitor (MAOI) (certain drugs for depression, psychiatric, or emotional conditions, or Parkinson’s disease), or for 2 weeks after stopping the MAOI drug. If you do not know if your prescription drug contains an MAOI, ask a doctor or pharmacist before taking this product.

Ask a doctor before use if you have
• a cough that occurs with too much phlegm (mucus)
• a cough that lasts or is chronic as occurs with smoking, asthma, or emphysema

Stop use and ask a doctor if cough lasts for more than 7 days, comes back, or is accompanied by fever, rash, or persistent headache. These can be signs of a serious condition.

If pregnant or breast-feeding, ask a health professional before use.

Keep out of reach of children.
Overdose warning: In case of overdose, get medical help or contact a Poison Control Center right away. Prompt medical attention is critical for adults as well as children even if you do not notice any signs or symptoms.

Directions

• do not take more than 8 softgels in any 24-hour period
• this adult product is not intended for use in children under 12 years of age

adults and children 12 years and over | take 2 softgels every 6 to 8 hours, as needed
children under 12 years | do not use

Other information

• store at 20°-25°C(68°-77°F)
• avoid excessive heat above 40°C(104°F)
• protect from light

Inactive ingredients

edible white ink, FD&C blue #1, FD&C red #40, gelatin, glycerin, isopropyl alcohol, medium chain triglycerides, polyethylene glycol, povidone, propyl gallate, propylene glycol, purified water, sorbitol sorbitan solution

Questions or comments?

1-888-577-8033 Monday-Friday 8am-4pm EST

Compare to the active ingredient in Robitussin® CoughGels®*

Adult
Long Acting Cough Relief

Relieves cough for up to 8 Hours
ages 12+

READ AND KEEP OUTER CARTON FOR COMPLETE WARNINGS AND PRODUCT INFORMATION

TAMPER EVIDENT: DO NOT USE IF IMPRINTED SEAL UNDER CAP IS BROKEN OR MISSING FROM BOTTLE

Distributed by: Strive Pharmaceuticals Inc.,
East Brunswick, NJ 08816

Product of UAE

Packaged and Quality Assured in the USA

*This product is not manufactured or distributed by Pfizer Consumer Healthcare, owner of the registered trademark Robitussin® CoughGels®.